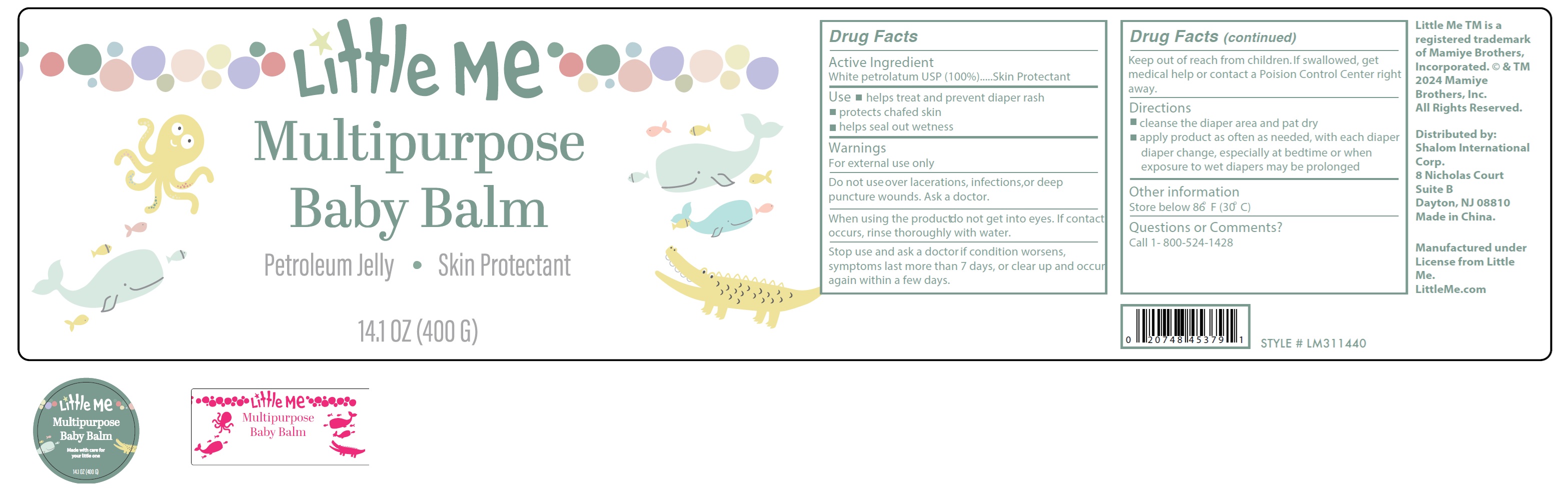 DRUG LABEL: Little Me Multipurpose Baby Balm
NDC: 73025-089 | Form: OINTMENT
Manufacturer: Shalom International Corp
Category: otc | Type: HUMAN OTC DRUG LABEL
Date: 20241211

ACTIVE INGREDIENTS: WHITE PETROLATUM 1000 mg/1 g

Little Me Multipurpose Baby Balm

Active Ingredient

White petrolatum USP (100%)

PURPOSE

Skin Protectant

Use

- helps treat and prevent diaper rash
- protects chafed skin
- helps seal out wetness

Warnings

For external use only

Do not use

over lacerations, infections,or deep puncture wounds. Ask a doctor.

When using the product

do not get into eyes. If contact occurs, rinse thoroughly with water.

Stop use and ask a doctor if

condition worsens, symptoms last more than 7 days, or clear up and occur again within a few days.

Keep out of reach from children.

If swallowed, get medical help or contact a Poision Control Center right away.

Directions

- cleanse the diaper area and pat dry
- apply product as often as needed, with each diaper diaper change, especially at bedtime or when exposure to wet diapers may be prolonged

Other information

Store below 86° F (30° C)

Questions or Comments?

Call 1- 800-524-1428